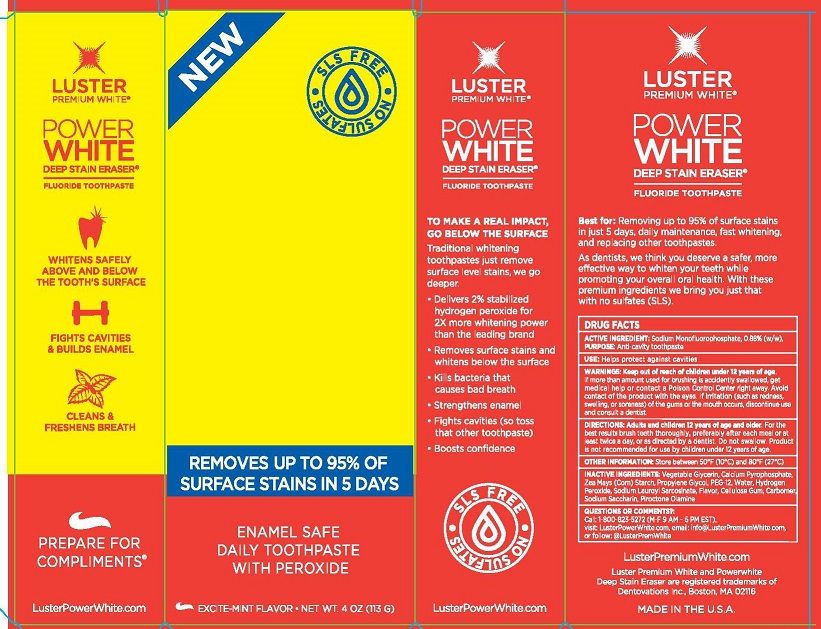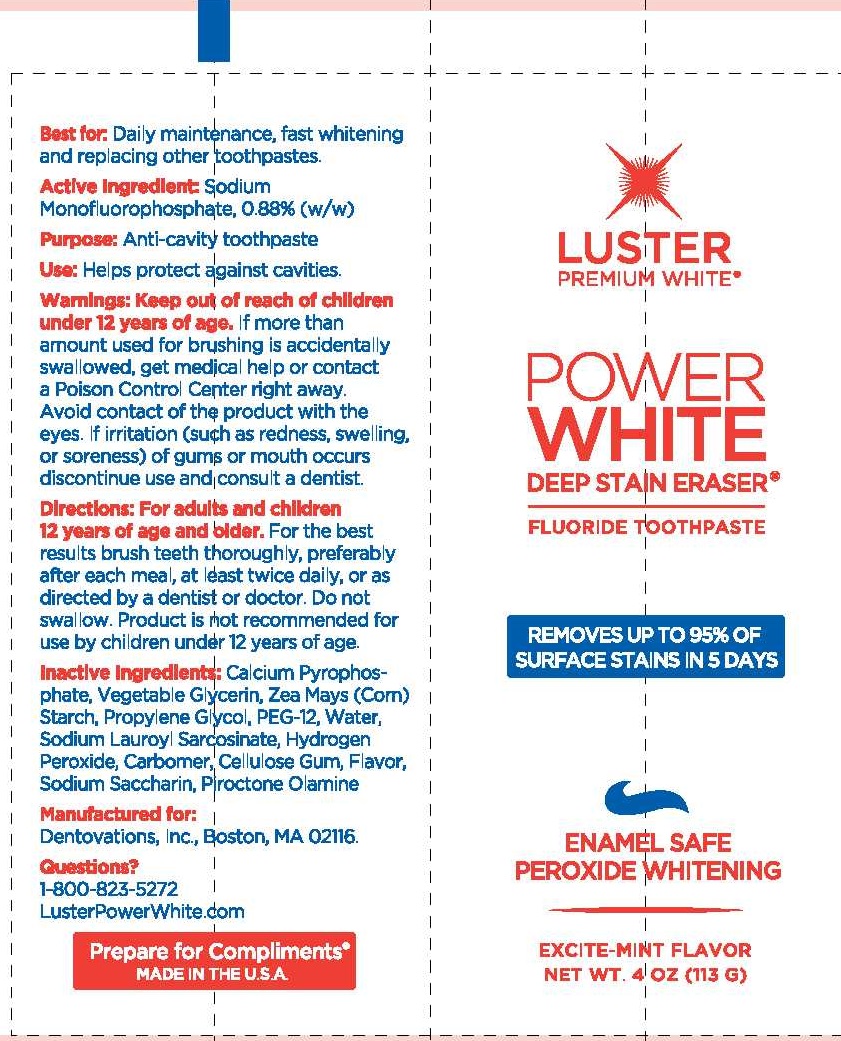 DRUG LABEL: ELECTRIFYING BLUE POLISH
NDC: 57353-105 | Form: GEL, DENTIFRICE
Manufacturer: DENTOVATIONS INC
Category: otc | Type: HUMAN OTC DRUG LABEL
Date: 20191230

ACTIVE INGREDIENTS: SODIUM FLUORIDE .24 g/100 g
INACTIVE INGREDIENTS: SORBITOL; HYDRATED SILICA; WATER; PROPYLENE GLYCOL; SODIUM LAURYL SULFATE; SODIUM PHOSPHATE, DIBASIC, ANHYDROUS; POLYVINYL ALCOHOL; CARBOXYMETHYLCELLULOSE SODIUM; SODIUM BENZOATE; ACESULFAME POTASSIUM; XANTHAN GUM; SODIUM PYROPHOSPHATE; TITANIUM DIOXIDE; FD&C BLUE NO. 1

ACTIVE INGREDIENT: SODIUM FLUORIDE 0.24% (W/W)

PURPOSE:

ANTI-CAVITY

INDICATIONS AND USAGE

USES: ANTI-CAVITY.

DOSAGE AND ADMINISTRATION

DIRECTIONS: ADULTS AND CHILDREN 12 YEARS OF AGE AND OLDER:

FOR THE BEST RESULTS BRUSH TEETH THOROUGHLY, PREFERABLY AFTER EACH MEAL OR AT LEAST TWICE A DAY, OR AS DIRECTED BY A DENTIST OR DOCTOR. DO NOT SWALLOW. PRODUCT IS NOT RECOMMENDED FOR USE BY CHILDREN UNDER 12 YEARS OF AGE.

KEEP OUT OF REACH OF CHILDREN UNDER 12 YEARS.

WARNINGS

WARNINGS: IF MORE THAN THE AMOUNT USED FOR BRUSHING IS ACCIDENTALLY SWALLOWED, GET MEDICAL HELP OR CONTACT A POISON CONTROL CENTER RIGHT AWAY. AVOID CONTACT OF THE PRODUCT WITH THE EYE. IF IRRITATION (SUCH AS REDNESS, SWELLING, SORENESS) OF THE GUM OR THE MOUTH OCCURS, DISCONTINUE USE AND CONSULT A DENTIST.

OTHER INFORMATION: STORE BETWEEN 59-80°F (15-27°C).

INACTIVE INGREDIENT

INACTIVE INGREDIENTS: Sorbitol, Silica, Water, Propylene Glycol, Sodium Lauryl Sulfate, Flavor, Disodium Phosphate, PVM/MA Copolymer,

Cellulose Gum, Sodium Benzoate, Potassium Acesulfame, Xanthan Gum, Tetrasodium Pyrophosphate, Titanium Dioxide, FD&C Blue No. 1

QUESTIONS OR COMMENTS?

1-800-823-5727 * M-F 9 A.M. - 5 P.M. EST * LUSTERPREMIUMWHITE.COM